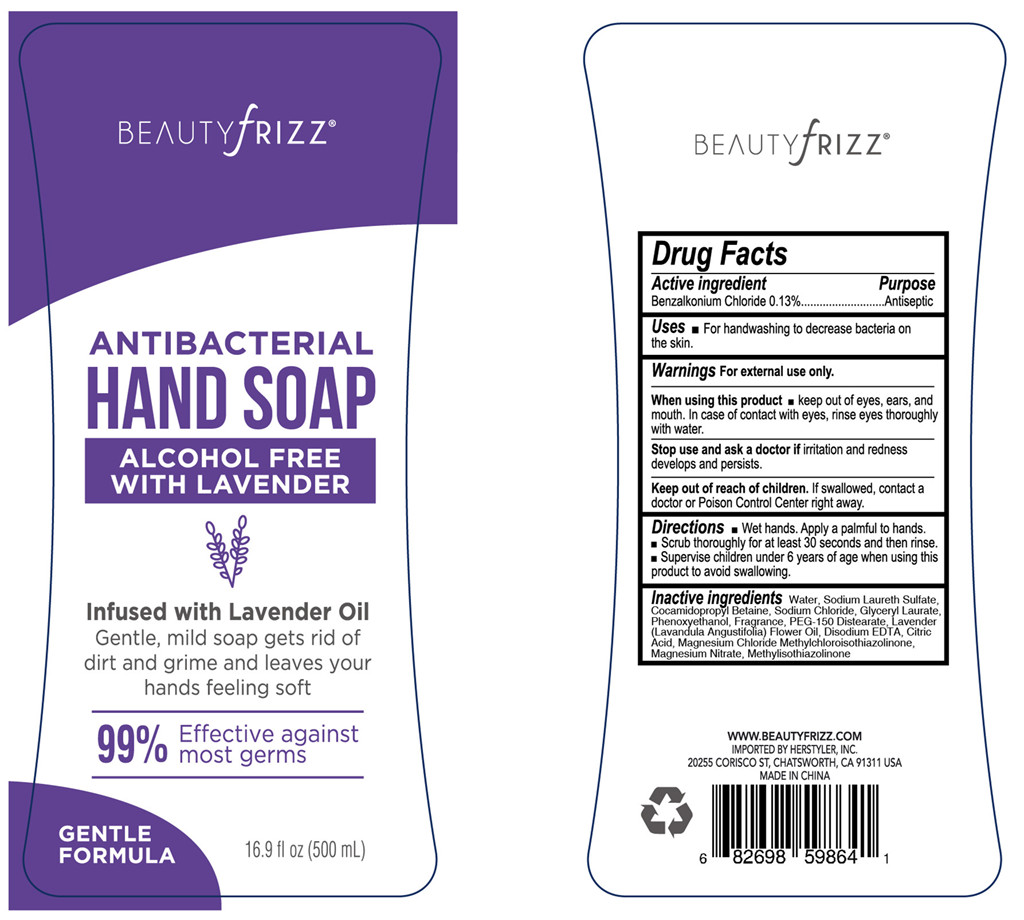 DRUG LABEL: Hand Antibacterial
NDC: 76383-029 | Form: LIQUID
Manufacturer: BBC GROUP LIMITED
Category: otc | Type: HUMAN OTC DRUG LABEL
Date: 20200523

ACTIVE INGREDIENTS: BENZALKONIUM CHLORIDE 1.3 mg/1 mL
INACTIVE INGREDIENTS: MAGNESIUM CHLORIDE; METHYLISOTHIAZOLINONE; GLYCERYL LAURATE; PHENOXYETHANOL; COCAMIDOPROPYL BETAINE; SODIUM LAURETH SULFATE; LAVENDER OIL; PEG-150 DISTEARATE; WATER; SODIUM CHLORIDE; MAGNESIUM NITRATE; EDETATE SODIUM; METHYLCHLOROISOTHIAZOLINONE; ANHYDROUS CITRIC ACID

Beautyfrizz Hand Sanitizer bzk Lavender

Active Ingredient

Benzalkonium Chloride 0.13%

Purpose

Antiseptic

Uses

■ For Handwashing to help reduce bacteria on the skin.

Warnings

For external use only.

When using this product

■ keep out of eyes, ears, and mouth. In case of contact with eyes, rinse eyes throughly with water.

Stop use and ask a doctor if

irritation and redness develops and persists.

Keep out of reach of children

If swallowed, contact a doctor or Poison Control Center right away.

Directions

■ Wet hands. Apply a palmful to hands. ■ Scrub thoroughly for at least 30 seconds and then rinse. ■ Supervise children under 6 years of age when using this product to avoid swallowing

Inactive ingredients

Water, Sodium Laureth Sulfate, Cocamidopropyl Betaine, Sodium Chloride, Glyceryl Laurate, Phenoxyethanol, Fragrance, PEG-150 Distearate, Lavender (Lavandula Angustifolia) Flower Oil, Disodium EDTA, Citric Acid, Magnesium Chloride, Methylchloroisothiazoline, Magnesium Nitrate, Methylisothiazolinone